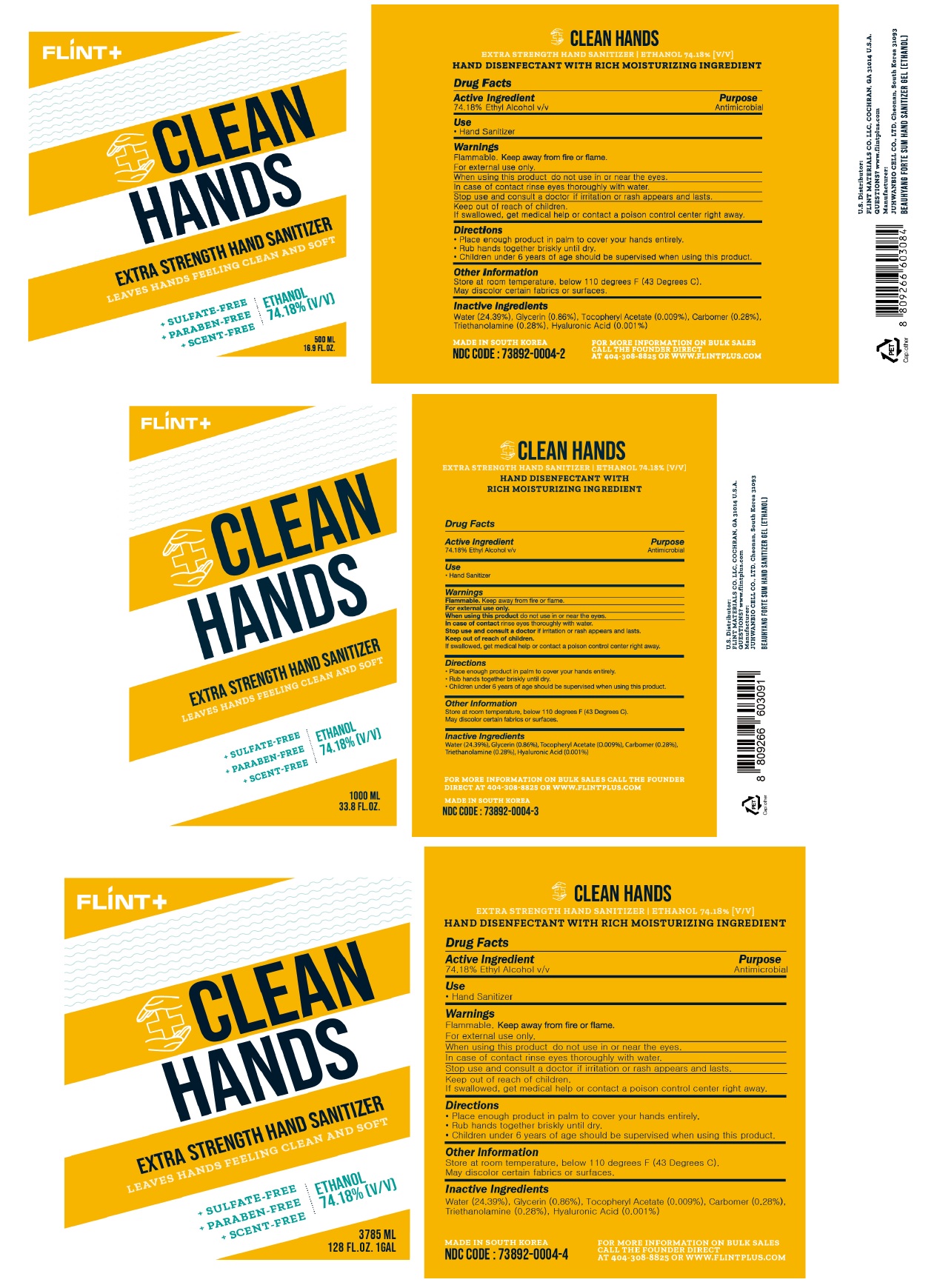 DRUG LABEL: Flint Clean Hands Hand Sanitizer Gel (Ethanol)
NDC: 73892-0004 | Form: GEL
Manufacturer: JUHWANBIO.CELL CO.,LTD.
Category: otc | Type: HUMAN OTC DRUG LABEL
Date: 20200514

ACTIVE INGREDIENTS: ALCOHOL 74.18 mL/100 mL
INACTIVE INGREDIENTS: WATER; GLYCERIN; .ALPHA.-TOCOPHEROL ACETATE; CARBOMER HOMOPOLYMER, UNSPECIFIED TYPE; TROLAMINE; HYALURONIC ACID

FLINT+ CLEAN HANDS EXTRA STRENGTH HAND SANITIZER

Active Ingredient

74.18% Ethyl Alcohol v/v

Purpose

Antimicrobial

Use

• Hand Sanitizer

Warnings

Flammable. Keep away from fire or flame.

For external use only.

When using this product do not use in or near the eyes.

In case of contact rinse eyes thoroughly with water.

Stop use and consult a doctor if irritation or rash appears and lasts.

Keep out of reach of children.

If swallowed, get medical help or contact a poison control center right away.

Directions

- Place enough product in palm to cover your hands entirely.
- Rub hands together briskly until dry.
- Children under 6 years of age should be supervised when using this product.

Other information

Store at room temperature, below 110 degrees F (43 Degrees C)

May discolor certain fabrics or surfaces.

Inactive Ingredients

Water (24.39 %), Glycerin (0.86 %), Tocopheryl Acetate (0.009 %), Carbomer (0.28 %), Triethanolamine (0.28 %), Hyaluronic Acid (0.001 %)

LEAVES HANDS FEELING CLEAN AND SOFT

+ SULFATE-FREE

+ PARABEN-FREE

+ SCENT-FREE

ETHANOL 74.18% [V/V]

HAND DISENFECTANT WITH RICH MOISTURIZING INGREDIENT

FOR MORE INFORMATION ON BULK SALES CALL THE FOUNDER DIRECT AT 404-308-8825 OR WWW.FLINTPLUS.COM

MADE IN SOUTH KOREA

U.S. Distributor:

FLINT MATERIALS CO. LLC, COCHRAN, GA 31014 U.S.A.

QUESTIONS? www.flintplus.com

Manufacturer:

JUHWANBIO CELL CO., LTD, Cheonan, South Korea 31093

BEAUHYANG FORTE SUM HAND SANITIZER GEL [ETHANOL]